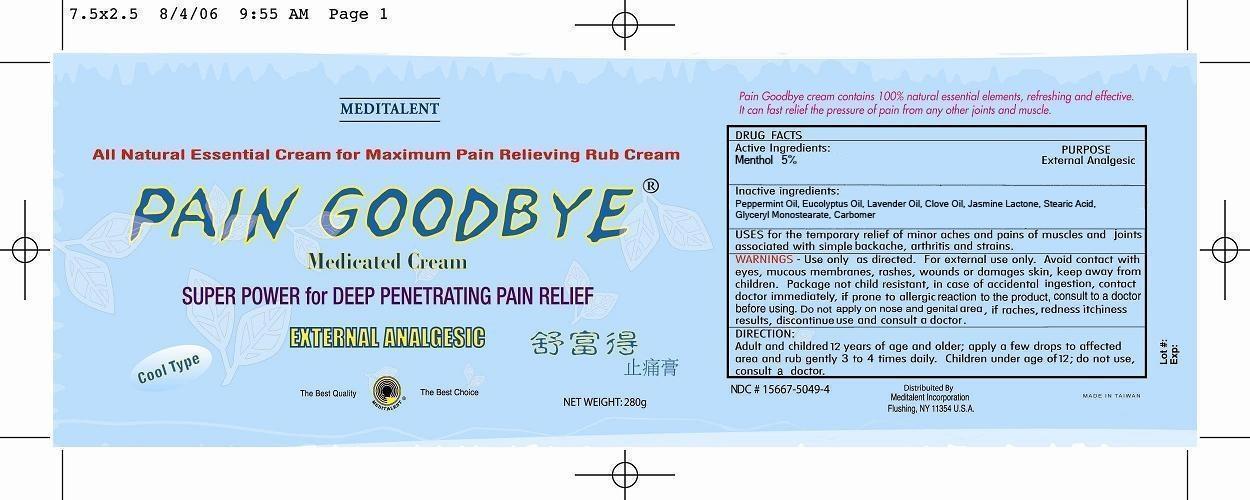 DRUG LABEL: PAIN GOODBYE MEDICATED CREAM
NDC: 15667-5049 | Form: CREAM
Manufacturer: Austin Biotechnology Inc
Category: otc | Type: HUMAN OTC DRUG LABEL
Date: 20131010

ACTIVE INGREDIENTS: MENTHOL 14 g/280 g
INACTIVE INGREDIENTS: PEPPERMINT OIL; EUCALYPTUS OIL; LAVENDER OIL; JASMINE LACTONE; STEARIC ACID; GLYCERYL MONOSTEARATE; CARBOMER 1342; CLOVE OIL

PAIN GOODBYE MEDICATED CREAM

ACTIVE INGREDIENTS

Menthol 5%

PURPOSE

Menthol External Analgesic

USES

Uses for the temporary relief of minor aches, and points of muscles and joints associated with simple backache, arthritis and strains.

WARNINGS

Use only as directed. For External Use Only. Avoid contact with eyes, mucous membrances, rashes, wounds or damaged skin. Package not child resistent, in case of accidental ingestion, contact doctor immediately.

WARNINGS

Keep out of reach of children.

WARNINGS

Do not apply on nose and genital area. If rashes, redness and itchness result, discontinue use and consult a doctor.

WARNINGS

If prone to allergic reaction to the product, consult a doctor before using.

DIRECTION

Adult and children 12 years of age and older; apply a few drops to affected area and rub gently 3 to 4 times daily. Children under age of 12, do not use, consult a doctor.

INACTIVE INGREDIENTS

Peppermint Oil, Eucolyptus Oil, Lavendor Oil, Clove oil, Jasmine Lactone, Stearic Acid, Glyceryl monostearate, Carbomer